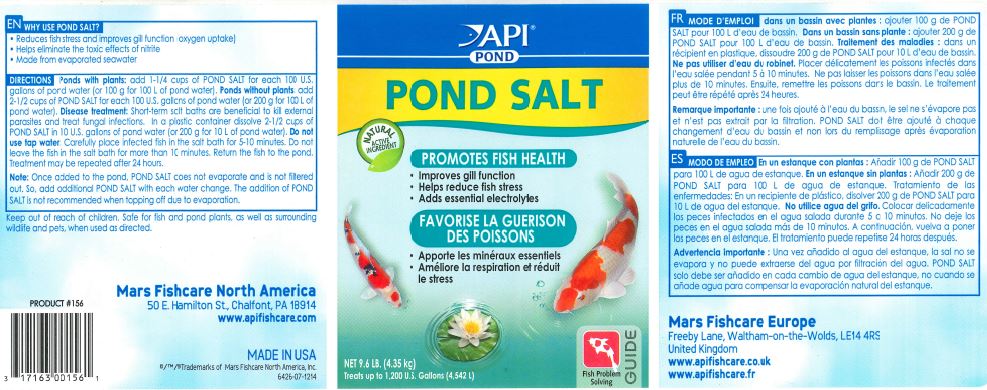 DRUG LABEL: API POND POND SALT
NDC: 17163-156 | Form: GRANULE, FOR SOLUTION
Manufacturer: MARS FISHCARE NORTH AMERICA, INC.
Category: animal | Type: OTC ANIMAL DRUG LABEL
Date: 20240923

ACTIVE INGREDIENTS: SODIUM CHLORIDE 100 g/100 g

Drug Facts

DESCRIPTION

WHY USE POND SALT?

Reduces fish stress and improves gill function (oxygen uptake)

Helps eliminate the toxic effects of nitrite

Made from evaporated seawater

DIRECTIONS

Ponds with plants: add 1-1/4 cups of POND SALT for each 100 U.S. gallons of pond water (or 100 g for 100 L of pond water).

Ponds without plants: add 2-1/2 cups of POND SALT for each 100 U.S. gallons of pond water (or 200 g for 100 L of pond water).

Disease treatment: Short-term salt baths are beneficial to kill external parasites and treat fungal infections. In a plastic container dissolve 2-1/2 cups of POND SALT in 10 U.S. gallons of pond water (or 200 g for 10 L of pond water). Do not use tap water. Carefully place infected fish in the salt bath for 5-10 minutes. Do not leave fish in the salt bath for more than 10 minutes. Return the fish to the pond. Treatment may be repeated after 24 hours.

Note: Once added to the pond, POND SALT does not evaporate and is not filtered out. So, add additional POND SALT with each water change. The addition of POND SALT is not recommended when topping off due to evaporation.

Keep out of reach of children.

Safe for fish and pond plants, as well as surrounding wildlife and pets, when used as directed.

PACKAGE LABEL

API

POND

POND SALT

NATURAL

ACTIVE

INGREDIENT

PROMOTES FISH HEALTH

Improves gill function

Helps reduce fish stress

Adds essential electrolytes

NET 9.6 LB. (4.35 kg)

Treats up to 1,200 U.S. Gallons (4,542 L)

Fish Problem

Solving

GUIDE